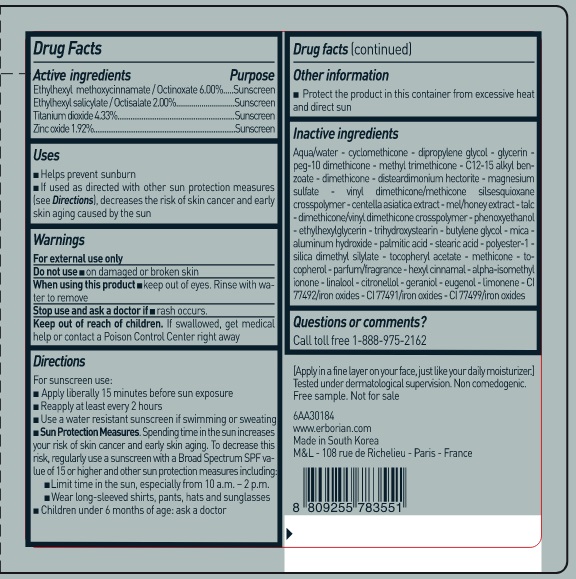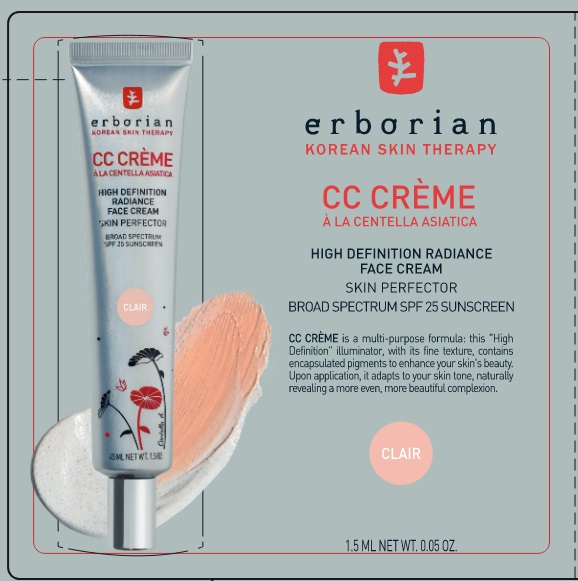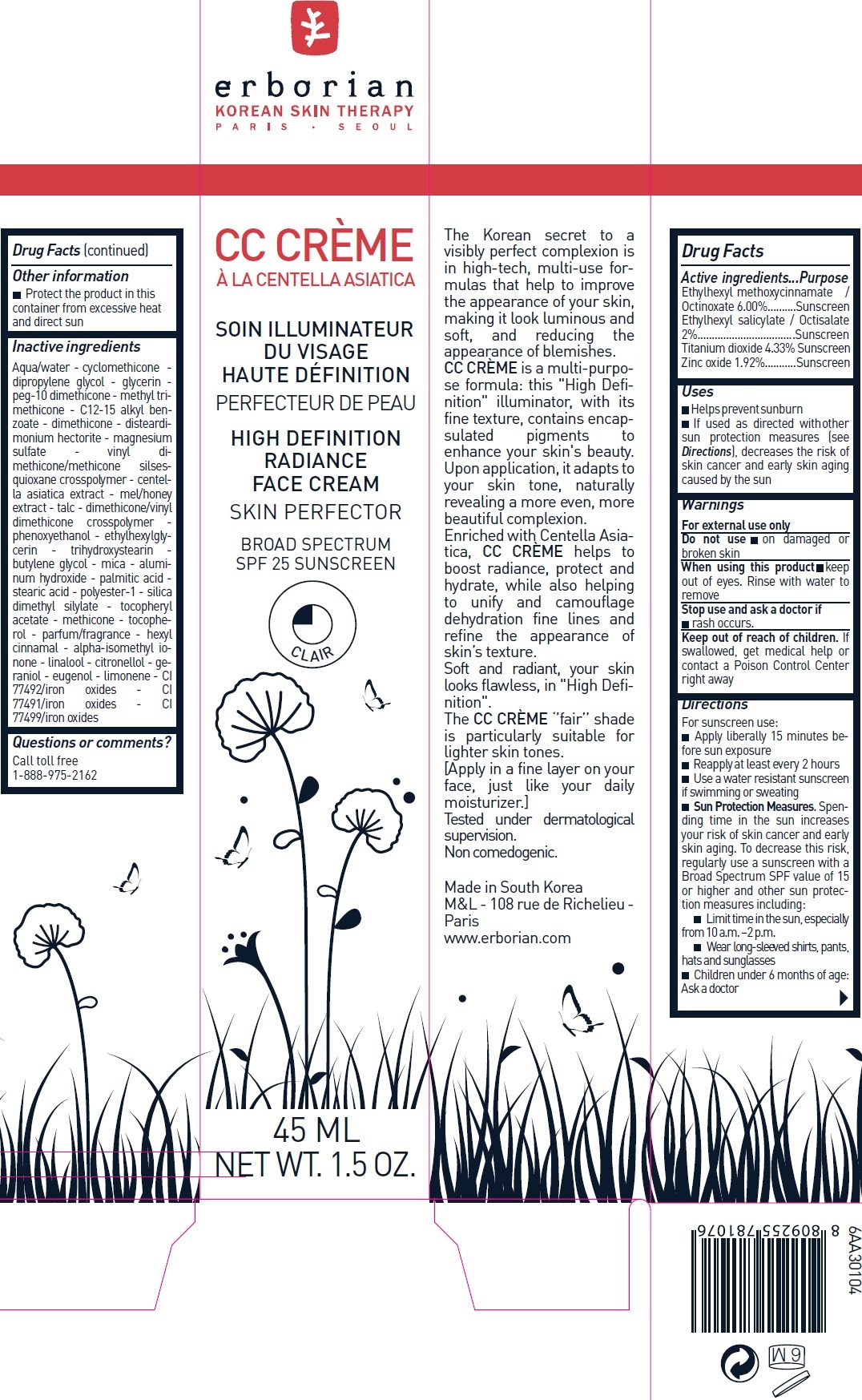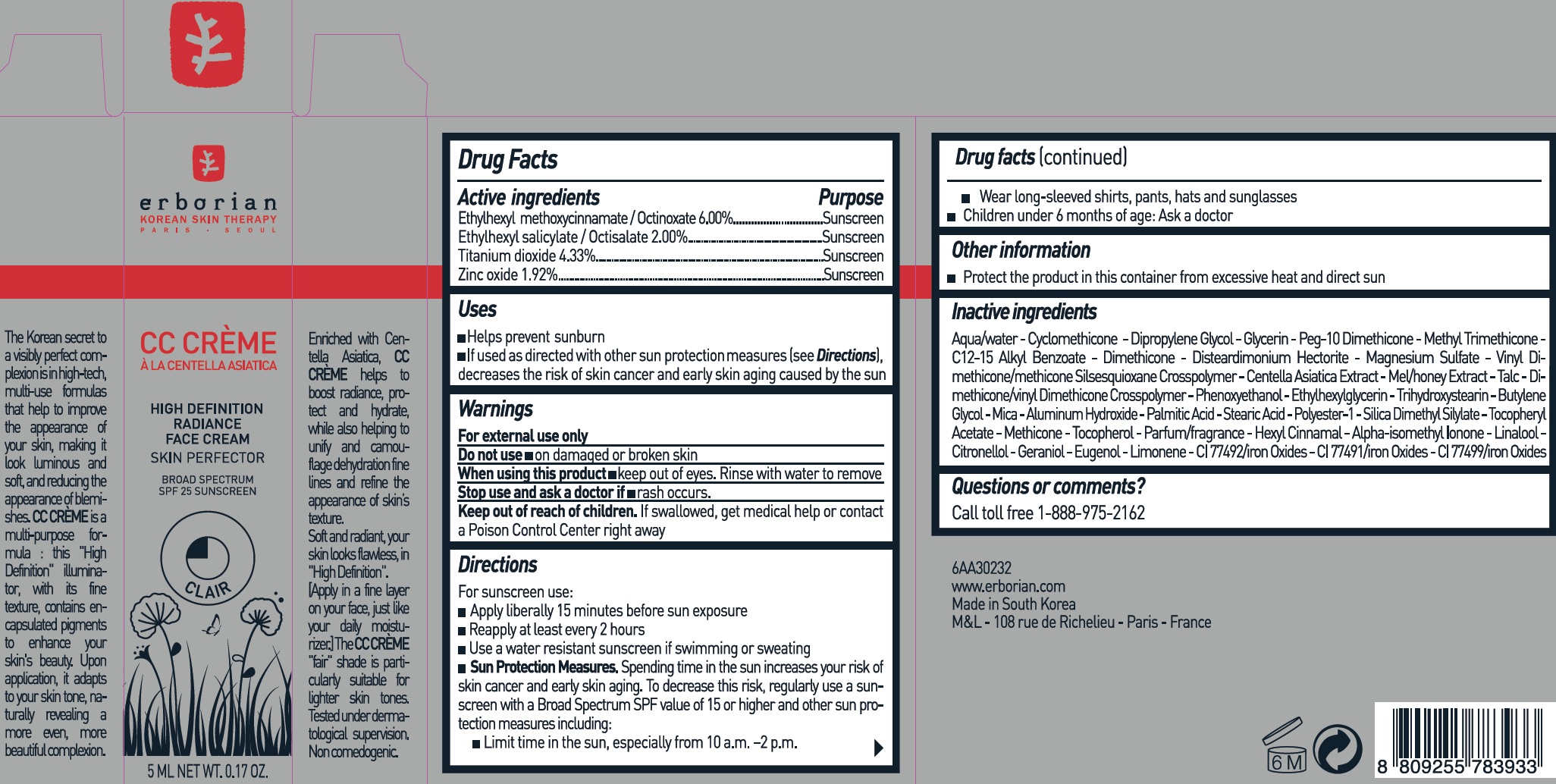 DRUG LABEL: ERBORIAN - CC CREME HIGH DEFINITION SPF25 CLAIR
NDC: 10345-911 | Form: CREAM
Manufacturer: LABORATOIRES M&L
Category: otc | Type: HUMAN OTC DRUG LABEL
Date: 20241211

ACTIVE INGREDIENTS: OCTISALATE 20 mg/1 mL; OCTINOXATE 60 mg/1 mL; TITANIUM DIOXIDE 43.3 mg/1 mL; ZINC OXIDE 19.2 mg/1 mL
INACTIVE INGREDIENTS: WATER; CYCLOMETHICONE; DIPROPYLENE GLYCOL; GLYCERIN; PEG-10 DIMETHICONE (600 CST); METHYL TRIMETHICONE; ALKYL (C12-15) BENZOATE; DIMETHICONE; DISTEARDIMONIUM HECTORITE; MAGNESIUM SULFATE, UNSPECIFIED; CENTELLA ASIATICA; TALC; PHENOXYETHANOL; ETHYLHEXYLGLYCERIN; TRIHYDROXYSTEARIN; BUTYLENE GLYCOL; MICA; ALUMINUM HYDROXIDE; PALMITIC ACID; STEARIC ACID; POLYESTER-10; SILICA DIMETHYL SILYLATE; .ALPHA.-TOCOPHEROL ACETATE; METHICONE (20 CST); TOCOPHEROL; .ALPHA.-HEXYLCINNAMALDEHYDE; ISOMETHYL-.ALPHA.-IONONE; LINALOOL, (+/-)-; .BETA.-CITRONELLOL, (R)-; GERANIOL; EUGENOL; LIMONENE, (+)-; FERRIC OXIDE YELLOW; FERRIC OXIDE RED; FERROSOFERRIC OXIDE

ERBORIAN - CC CREME HIGH DEFINITION SPF25 CLAIR

Active ingredients

Ethylhexyl methoxycinnamate / Octinoxate 6.00%

Ethylhexyl salicylate / Octisalate 2.00%

Titanium dioxide 4.33%

Zinc oxide 1.92%

Purpose

Sunscreen

Uses

- Helps prevent sunburn
- If used as directed with other sun protection measures (see Directions), decreases the risk of skin cancer and early skin aging caused by the sun

Warnings

For external use only

Do not use

- on damaged or broken skin

When using this product

- keep out of eyes. Rinse with water to remove

Stop use and ask a doctor if

- rash occurs.

Keep out of reach of children.

If swallowed, get medical help or contact a Poison Control Center right away

Directions

For sunscreen use:

- Apply liberally 15 minutes before sun exposure
- Reapply at least every 2 hours
- Use a water resistant sunscreen if swimming or sweating
- Sun Protection Measures. Spending time in the sun increases your risk of skin cancer and early skin aging. To decrease this risk, regularly use a sunscreen with a Broad Spectrum SPF value of 15 or higher and other sun protection measures including:
- Limit time in the sun, especially from 10 a.m. –2 p.m.
- Wear long-sleeved shirts, pants, hats and sunglasses
- Children under 6 months of age: Ask a doctor

Other information

- Protect the product in this container from excessive heat and direct sun

Inactive ingredients

Aqua/Water - Cyclomethicone - Dipropylene Glycol - Glycerin - Peg- 10 Dimethicone - Methyl Trimethicone - C12- 15 Alkyl Benzoate - Dimethicone - Disteardimonium Hectorite - Magnesium Sulfate - Vinyl Dimethicone/Methicone Silsesquioxane Crosspolymer - Centella Asiatica Extract - Mel/Honey Extract - Talc - Dimethicone/Vinyl Dimethicone Crosspolymer -Phenoxyethanol - Ethylhexylglycerin - Trihydroxystearin - Butylene Glycol - Mica - Aluminum Hydroxide - Palmitic Acid - Stearic Acid - Polyester- 1 - Silica Dimethyl Silylate - Tocopheryl Acetate - Methicone - Tocopherol - Parfum/Fragrance - Hexyl Cinnamal - Alpha-Isomethyl Ionone - Linalool - Citronellol - Geraniol - Eugenol - Limonene - Cl 77492/Iron Oxides - Cl77491/Iron Oxides - Cl77499/Iron Oxides

Questions or comments?

Call toll free 1-888-975-2162